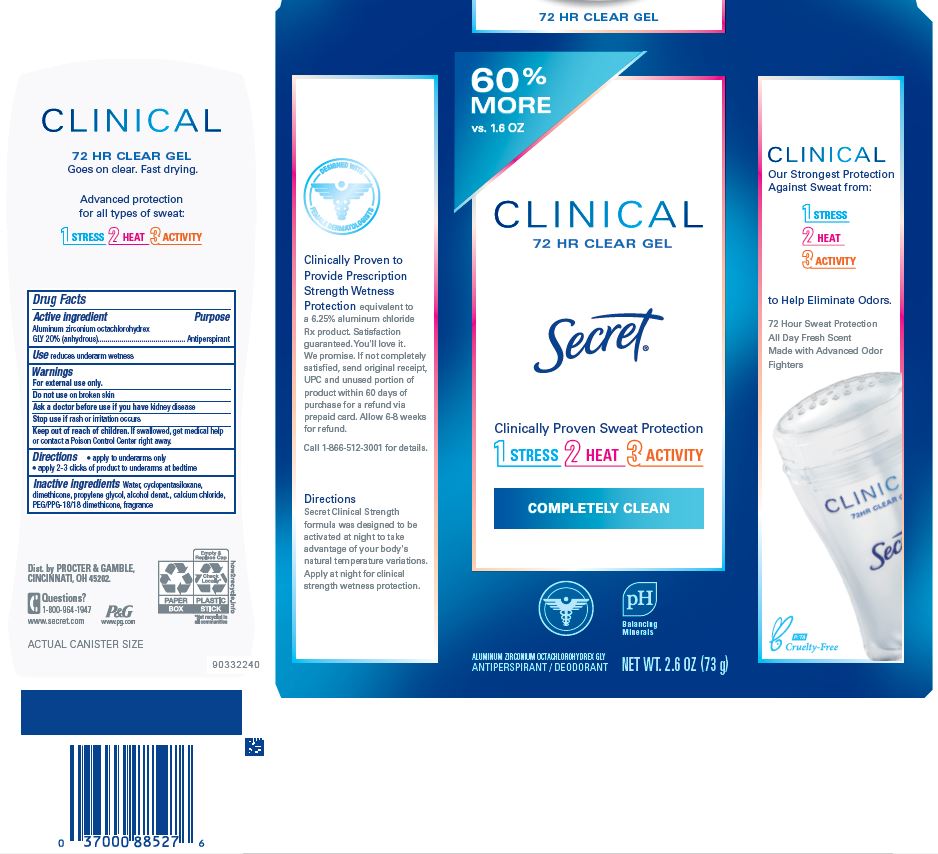 DRUG LABEL: Secret Clinical Clear
NDC: 69423-693 | Form: GEL
Manufacturer: The Procter & Gamble Manufacturing Company
Category: otc | Type: HUMAN OTC DRUG LABEL
Date: 20251231

ACTIVE INGREDIENTS: ALUMINUM ZIRCONIUM OCTACHLOROHYDREX GLY 20 g/100 g
INACTIVE INGREDIENTS: ALCOHOL; PROPYLENE GLYCOL; WATER; CYCLOPENTASILOXANE; DIMETHICONE; CALCIUM CHLORIDE; PEG/PPG-18/18 DIMETHICONE

Secret® Clinical Clear Completely Clean

Drug Facts

Active ingredient

Aluminum zirconium octachlorohydrex Gly 20% (anhydrous)

Purpose

Antiperspirant

Use

- reduces underarm wetness

Warnings

For external use only.

Do not use on broken skin

Ask a doctor before use if you have kidney disease

Stop use if rash or irritation occurs

Keep out of reach of children. If swallowed, get medical help or contact a Poison Control Center right away.

Directions

- apply to underarms only
- apply 2-3 clicks of product to underarms at bedtime

Inactive ingredients

water, cyclopentasiloxane, dimethicone, propylene glycol, alcohol denat., calcium chloride, PEG/PPG-18/18 dimethicone, fragrance

Questions?

1-800-964-1947

www.secret.com

Dist. by PROCTER & GAMBLE,
CINCINNATI, OH 45202.

PRINCIPAL DISPLAY PANEL - 73 g Canister Carton

CLINICAL

Secret ®

72 HR CLEAR GEL

Clinically Proven Sweat Protection

COMPLETELY CLEAN

ALUMINUM ZIRCONIUM OCTACHLOROHYDREX GLY
ANTIPERSPIRANT / DEODORANT

NET WT. 2.6 OZ (73 g)